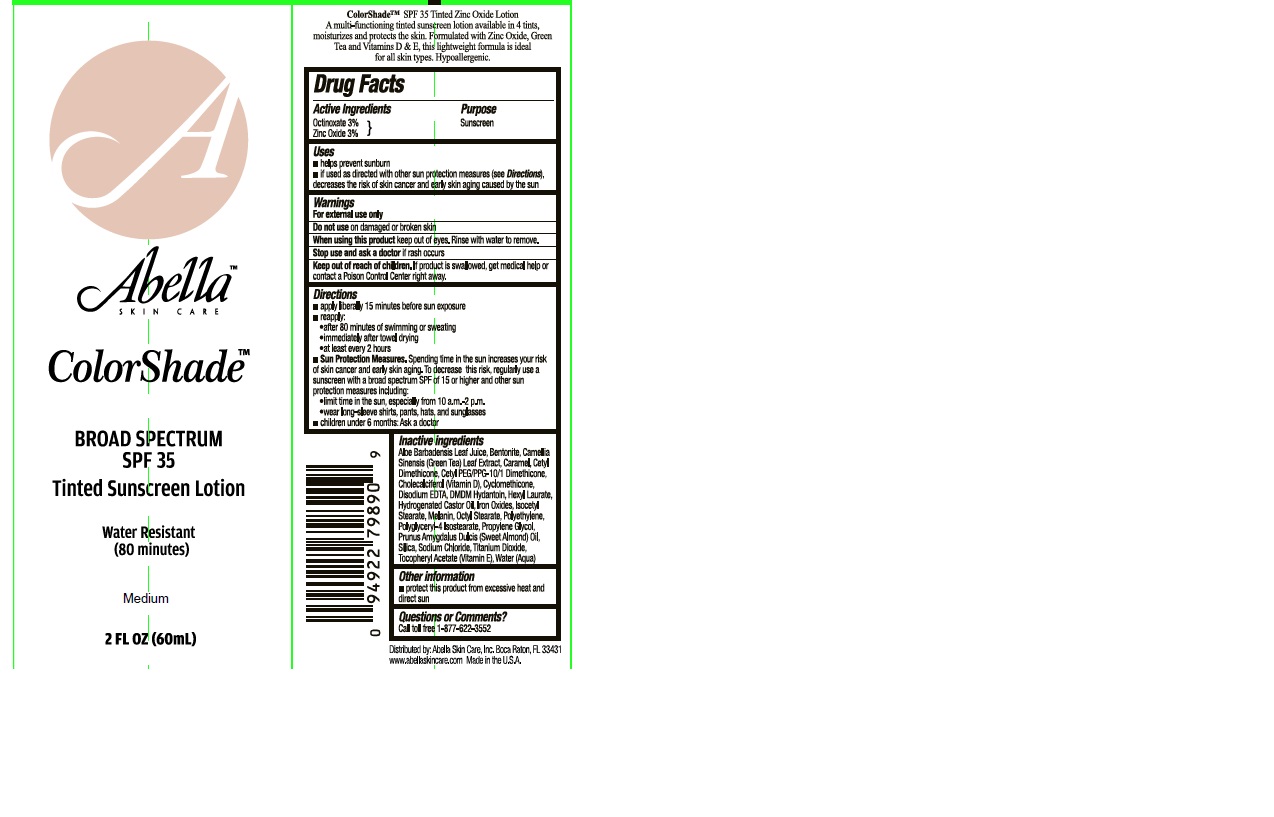 DRUG LABEL: Abella
NDC: 58443-0195 | Form: LOTION
Manufacturer: Prime Enterprises Inc.
Category: otc | Type: HUMAN OTC DRUG LABEL
Date: 20200117

ACTIVE INGREDIENTS: ZINC OXIDE 29.4 mg/1 mL; OCTINOXATE 29.4 mg/1 mL
INACTIVE INGREDIENTS: SODIUM CHLORIDE; ALMOND OIL; SILICON DIOXIDE; GREEN TEA LEAF; BENTONITE; TITANIUM DIOXIDE; CARAMEL; CETYL DIMETHICONE 45; CETYL PEG/PPG-10/1 DIMETHICONE (HLB 2); CHOLECALCIFEROL; HIGH DENSITY POLYETHYLENE; CYCLOMETHICONE; PROPYLENE GLYCOL; DMDM HYDANTOIN; HEXYL LAURATE; HYDROGENATED CASTOR OIL; FERRIC OXIDE RED; ISOCETYL STEARATE; MELANIN SYNTHETIC (TYROSINE, PEROXIDE); WATER; ALOE VERA LEAF; .ALPHA.-TOCOPHEROL ACETATE; EDETATE DISODIUM; OCTYL STEARATE; POLYGLYCERYL-4 ISOSTEARATE; TRIETHOXYCAPRYLYLSILANE

Abella Skin Care Inc. ColorShade SPF 35 Tinted Sunscreen Lotion - Medium

Active Ingredients

Octinoxate 3%

Zinc Oxide 3%

Purpose

Sunscreen

Uses

- helps prevent sunburn
- if used as directed with other sun protection measures (see Directions), decreases the risk of skin cancer and early skin aging caused by the sun

Warnings

For external use only

Do not use on damaged or broken skin

When using this product keep out of eyes.

Rinse with water to remove.

Stop use and ask a doctor if rash occurs.

Keep out of reach of children. If product is swallowed, get medical help or contact a Poison Control Center right away.

Directions

- apply liberally 15 minutes before sun exposure
- reapply:
- after 80 minutes of swimming or sweating
- immediately after towel drying
- at least every 2 hours
- Sun protection measures. Spending time in the sun increases your risk of skin cancer and early skin aging. To decrease this risk, regularly use a sunscreen spectrum SPF of 15 or higher and other sun protection measures including:
- limit time in the sun, especially from 10 a.m. - 2 p.m
- wear long-sleeved shirts, pants, hats, and sunglasses
- children under 6 months: Ask a doctor

Inactive Ingredients

Aloe Barbadensis Leaf Juice, Bentonite, Camellia Sinensis (Green Tea) Leaf Extract, Caramel, Cetyl Dimethicone, Cetyl PEG/PPG-10/1 Dimethicone, Cholecalciferol, Cyclomethicone, Disodium EDTA, DMDM Hydantoin, Hexyl Laurate, Hydrogenated Castor Oil, Iron Oxides, Isocetyl Stearate, Melanin, Octyl Stearate, Polyethylene, Polyglyceryl-4 Isostearate, Propylene Glycol, Prunus Amygdalus Dulcis (Sweet Almond) Oil, Silica, Sodium Chloride, Titanium Dioxide, Tocopheryl Acetate, Water (Aqua)

Other Information

- protect this product from excessive heat and direct sun

Questions or comments?

- Call toll free 1-877-622-3552